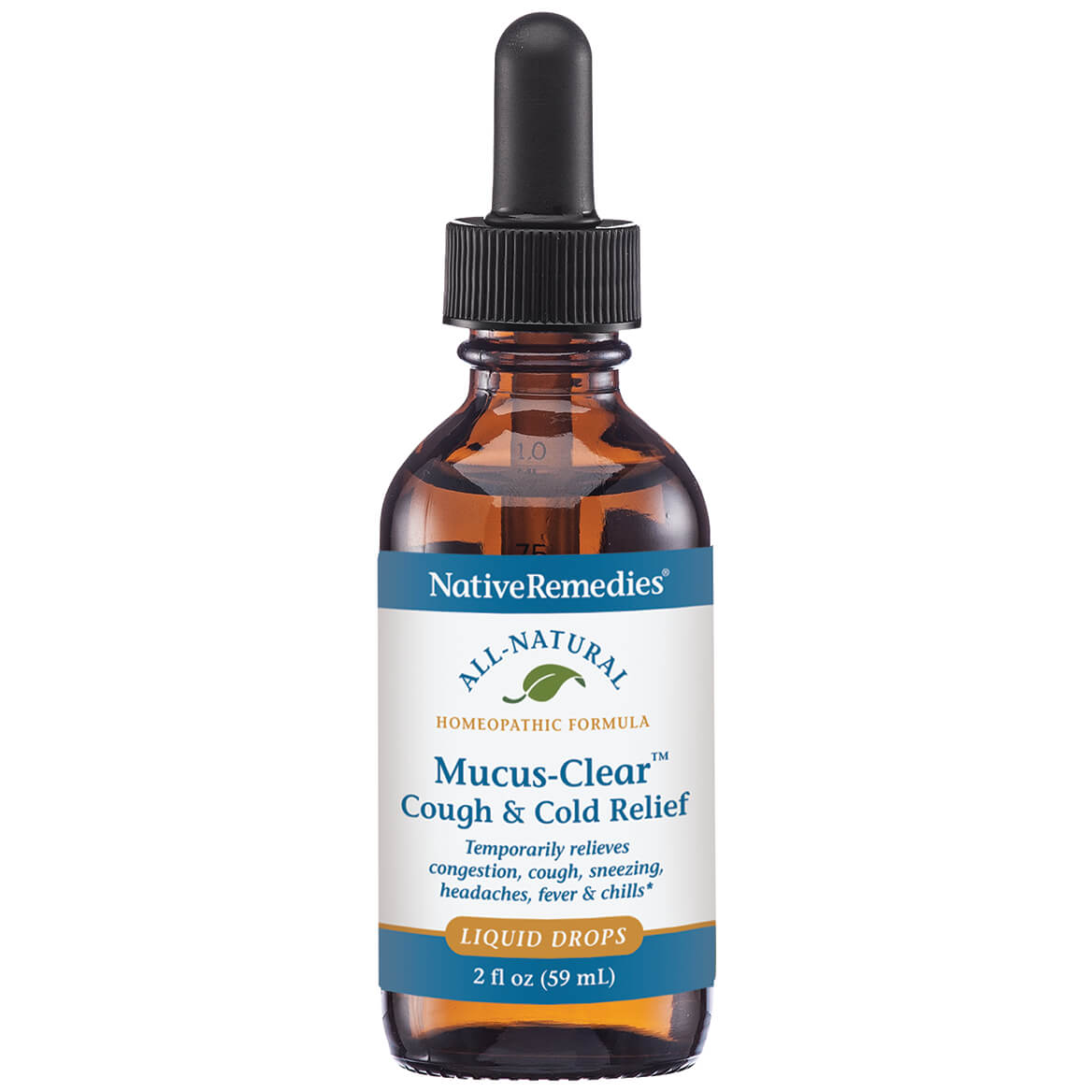 DRUG LABEL: Mucus Clear Cough and Cold Relief
NDC: 68703-385 | Form: LIQUID
Manufacturer: Silver Star Brands
Category: homeopathic | Type: HUMAN OTC DRUG LABEL
Date: 20250101

ACTIVE INGREDIENTS: SOLANUM DULCAMARA STEM 30 [hp_X]/59 mL; ECHINACEA ANGUSTIFOLIA 30 [hp_X]/59 mL; ZINC OXIDE 30 [hp_X]/59 mL; ZINC VALERATE DIHYDRATE 30 [hp_X]/59 mL; PHOSPHORUS 30 [hp_X]/59 mL; POTASSIUM DICHROMATE 30 [hp_X]/59 mL; POTASSIUM CHLORIDE 30 [hp_X]/59 mL; MERCURIC CHLORIDE 30 [hp_X]/59 mL; PULSATILLA PATENS WHOLE 30 [hp_X]/59 mL; POLYGALA SENEGA ROOT 30 [hp_X]/59 mL; SILVER 30 [hp_X]/59 mL; ECHINACEA PURPUREA 30 [hp_X]/59 mL; BAPTISIA TINCTORIA WHOLE 30 [hp_X]/59 mL; BRYONIA ALBA ROOT 30 [hp_X]/59 mL; CAUSTICUM 30 [hp_X]/59 mL; ARSENIC TRIOXIDE 30 [hp_X]/59 mL
INACTIVE INGREDIENTS: WATER; ANHYDROUS CITRIC ACID; POTASSIUM SORBATE

NativeRemedies® Mucus-Clear™ Cough & Cold Relief

HPUS Active Ingredients: Equal volumes of each ingredient in a 10X, 15X, and 30X potency: Arg met, Arsenicum alb, Baptisia, Bryonia,Causticum, Dulcamara, Echinacea angustifolia, Echinacea purp, Kali bic, Kali mur, Merc corros, Phos, Pulsatilla nutt, Senega, Zinc pic, Zinc val.

Uses*

Uses*: Temporarily relieves symptoms contributing to congestion, coughs, sneezing, headaches, fever & chills.

*Claims based on traditional homeopathic practice, not accepted medical evidence. Not FDA evaluated.

Warnings

Warnings: If symptoms persist or worsen, consult a healthcare professional. If pregnant or breastfeeding, ask a health professional before use. Keep this and all medication out of reach of children. In case of overdose, get medical help or contact a Poison Control Center right away.

Directions

Directions: Mix drops in 1/4 cup of water and sip slowly. Adults and children 12+: 0.25 mL 3-5 times daily. For accute symptoms, repeat every 15-20 minutes as needed up to 6 doses.

OTHER SAFETY INFORMATION

Contains no artificial flavors or colorants. No gluten added.

Tamper resistant for your protection. Use only if safety seal is intact.

Inactive ingredients

Inactive Ingredients: Citric acid, Potassium sorbate, Purified water

KEEP OUT OF REACH OF CHILDREN

Keep this and all medication out of reach of children.

PREGNANCY OR BREAST FEEDING

I pregnant or breastfeeding, ask a health professional before use.

PURPOSE

Temporarily relieves congestion, cough, sneezing, headaches, fever & chills.